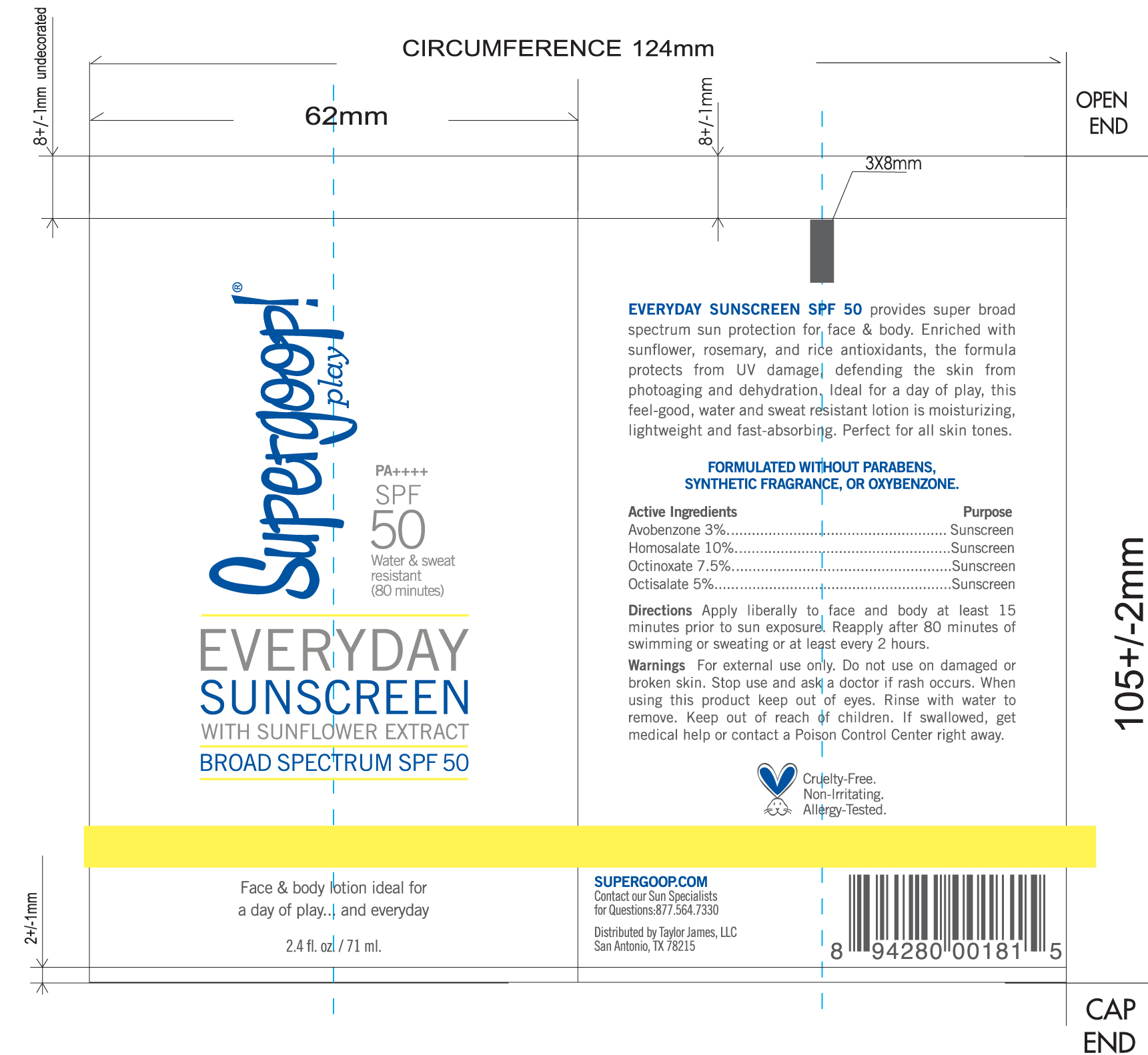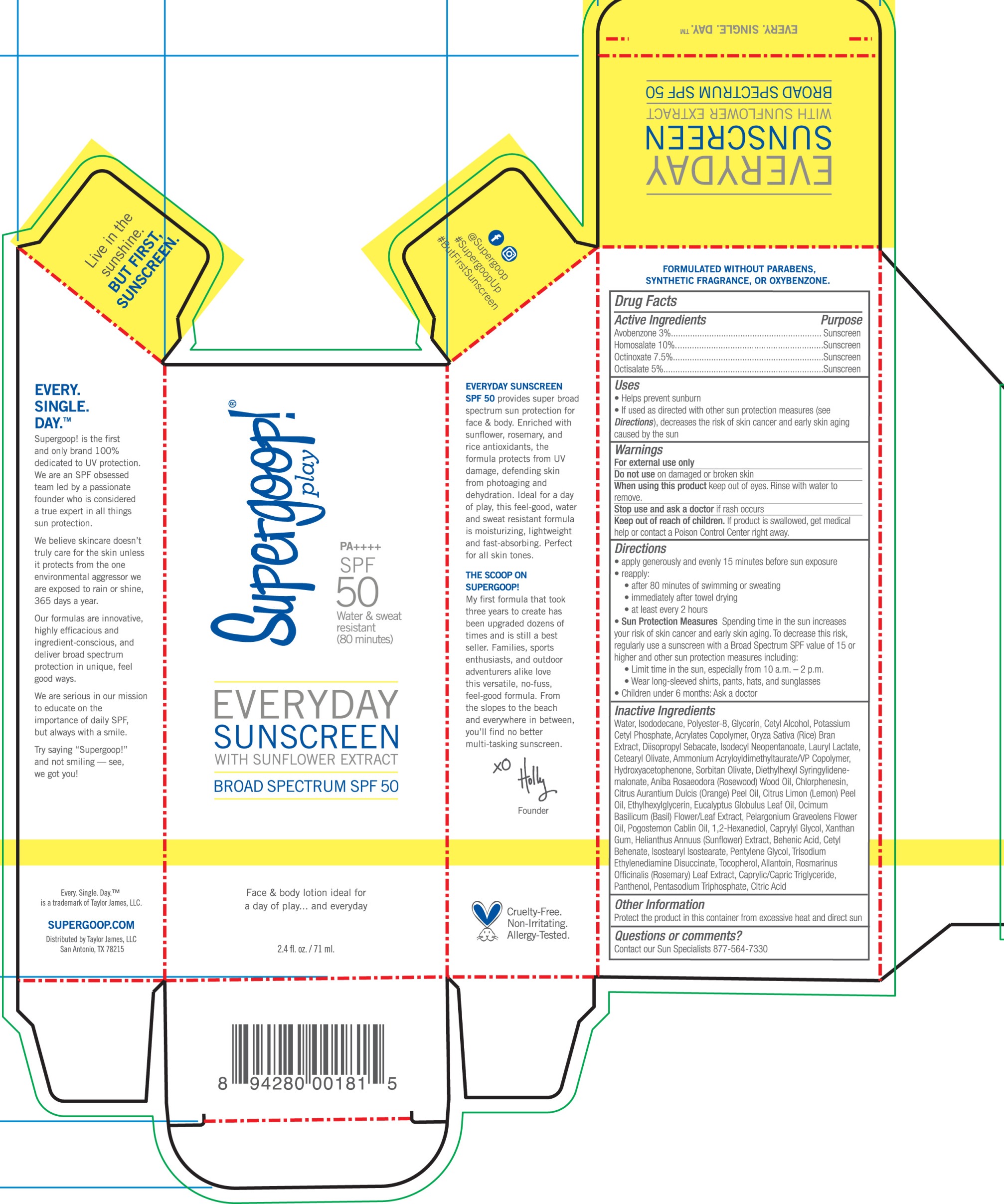 DRUG LABEL: Everyday Sunscreen SPF 50
NDC: 75936-235 | Form: CREAM
Manufacturer: Taylor James
Category: otc | Type: HUMAN OTC DRUG LABEL
Date: 20180706

ACTIVE INGREDIENTS: AVOBENZONE 3 g/100 mL; OCTINOXATE 7.5 g/100 mL; OCTISALATE 5 g/100 mL; HOMOSALATE 10 g/100 mL
INACTIVE INGREDIENTS: MEDIUM-CHAIN TRIGLYCERIDES; ROSEMARY; HELIANTHUS ANNUUS FLOWERING TOP; BEHENIC ACID; CETYL BEHENATE; ISOSTEARYL ISOSTEARATE; PENTYLENE GLYCOL; TOCOPHEROL; PANTHENOL; ISODODECANE; CETYL ALCOHOL; WATER; AMMONIUM ACRYLOYLDIMETHYLTAURATE/VP COPOLYMER; DIETHYLHEXYL SYRINGYLIDENEMALONATE; ROSEWOOD OIL; CHLORPHENESIN; ETHYLHEXYLGLYCERIN; OCIMUM BASILICUM FLOWERING TOP; DIISOPROPYL SEBACATE; ISODECYL NEOPENTANOATE; CETEARYL OLIVATE; HYDROXYACETOPHENONE; SORBITAN OLIVATE; ORANGE OIL; EUCALYPTUS OIL; PATCHOULI OIL; 1,2-HEXANEDIOL; CAPRYLYL GLYCOL; XANTHAN GUM; ALLANTOIN; GLYCERIN; POLYESTER-8 (1400 MW, CYANODIPHENYLPROPENOYL CAPPED); RICE BRAN; LAURYL LACTATE; LEMON OIL; PELARGONIUM GRAVEOLENS FLOWER OIL; POTASSIUM CETYL PHOSPHATE; TRISODIUM ETHYLENEDIAMINE DISUCCINATE; SODIUM TRIPOLYPHOSPHATE ANHYDROUS; CITRIC ACID MONOHYDRATE

Everyday Sunscreen SPF 50

Active Ingredients Purpose

Avobenzone 3% Sunscreen

Homosalate 10% Sunscreen

Octinoxate 7.5% Sunscreen

Octisalate 5% Sunscree

PURPOSE

Uses Helps Prevent Sunburn

If used as directed with other sun protection measures (see Directions), decreases the risk of Skin cancer and early skin aging caused by the sun

Keep out of reach of children.

Stop use and ask a doctor if rash occurs

WARNINGS

For External use only

Do not use on damaged or broken skin

When using this product, Keep out of eyes. Rinse with water to remove

If swallowed, get medical help or contact a Poison Control Center right away

Directions

- Apply liberally 15 minutes before sun exposure

Reapply:

- after 80 minutes of swimming or sweating
- immediately after towel drying
- at least every 2 hours
- Sun Protection Measures. Spending time in the sun increases your risk of skin

cancer and early skin aging. To decrease this risk, regularly use a sunscreen
with broad spectrum SPF of 15 or higher and other sun protection measures
including:

- limit time in the sun, especially from 10 a.m. - 2 p.m.
- Wear Long-sleeved shirts, pants, hats, and sunglasses
- Children under 6 months: Ask a doctor

INACTIVE INGREDIENT

Water, Isododecane, Polyester-8, Glycerin, Cetyl Alcohol, Potassium Cetyl Phosphate, Acrylates Copolymer, Oryza Sativa (Rice) Bran Extract, Diisopropyl Sebacate, Isodecyl Neopentanoate, Lauryl Lactate, Cetearyl Olivate, Ammonium Acryloyldimethyltaurate/VP Copolymer, Hydroxyacetophenone, Sorbitan Olivate, Diethylhexyl Syringylidenemalonate, Aniba Rosaeodora (Rosewood) Wood Oil, Chlorphenesin, Citrus Aurantium Dulcis (Orange) Peel Oil, Citrus Limon (Lemon) Peel Oil, Ethylhexylglycerin, Eucalyptus Globulus Leaf Oil, Ocimum Bascilicum (Basil) Flower/Leaf Extract, Pelargonium Graveolens Flower Oil, Pogostemon Cablin Oil, 1,2-hexanediol, Caprylyl Glycol, Xanthan Gum, Helianthus Annuus (Sunflower) Extract, Behenic Acid, Cetyl Behenate, Isostearyl Isostearate, Pentylene Glycol, Trisodium Ethylenediamene Disuccinate, Tocopheryl, Allantoin, Rosmarinus Officinalis (Rosemary) Leaf Extract, Caprylic/Capric Triglyceride, Panthenol, Pentasodium Triphosphate, Citric Acid

PACKAGE LABEL

Everyday Sunscreen with Sunflower Extract

Broad Spectrum SPF 50

2.4 fl. oz./ 71 ml